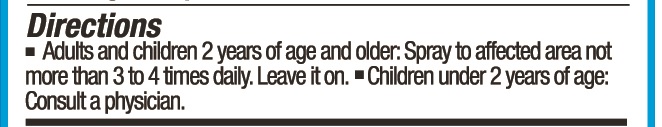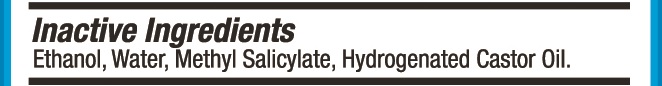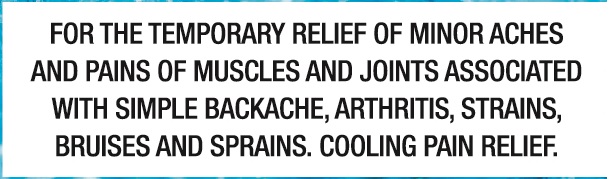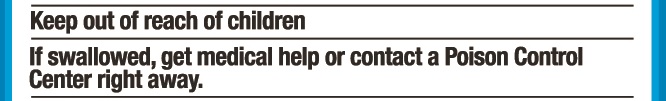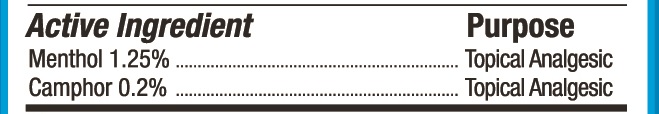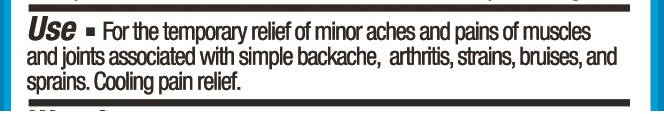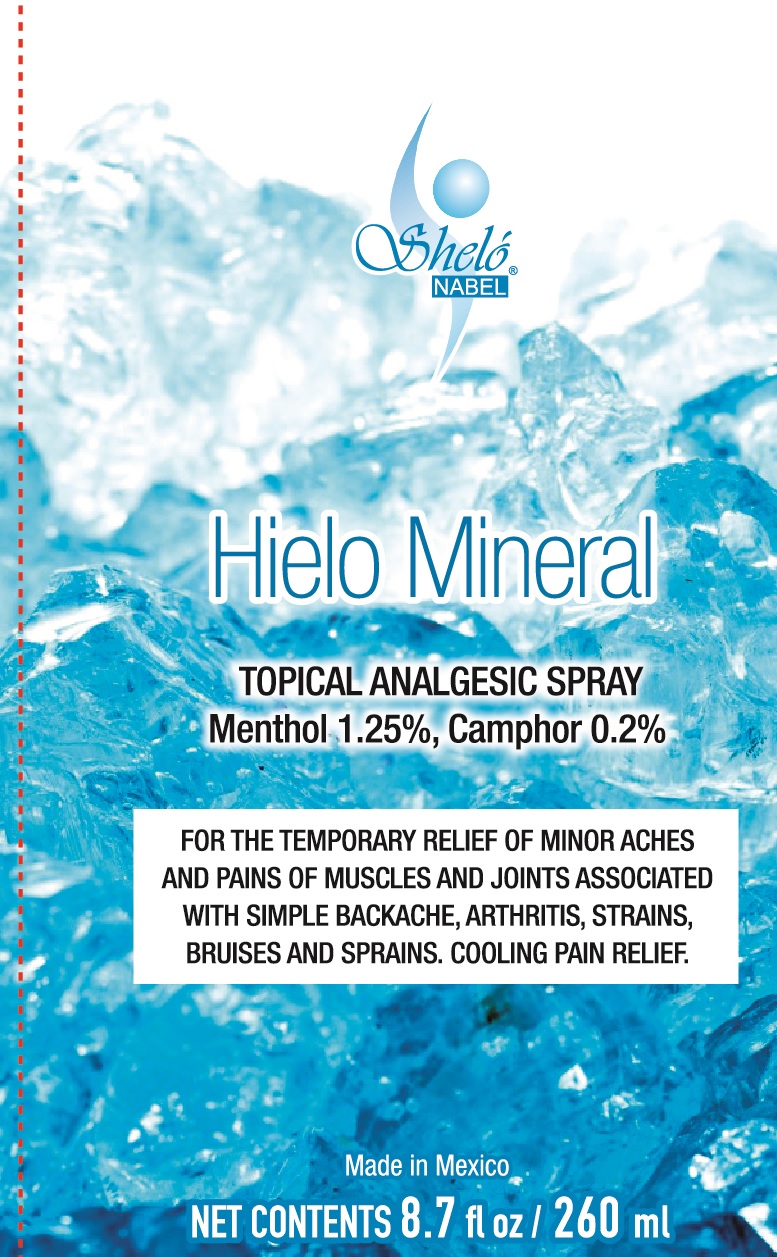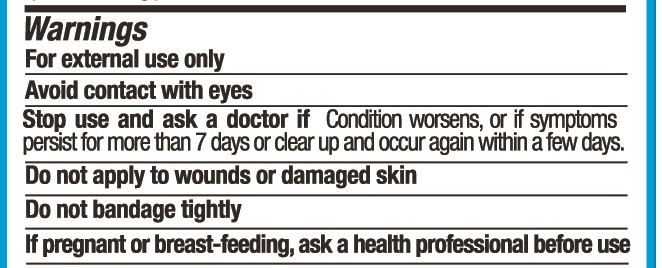 DRUG LABEL: Shelo NABEL Hielo Mineral
NDC: 71424-1060 | Form: SPRAY
Manufacturer: Corporativo Serysi S de R L de C V
Category: otc | Type: HUMAN OTC DRUG LABEL
Date: 20191015

ACTIVE INGREDIENTS: CAMPHOR (SYNTHETIC) 2 mg/1 g; MENTHOL, UNSPECIFIED FORM 12.5 mg/1 g
INACTIVE INGREDIENTS: DIMETHYL SALICYLATE

Sheló NABEL Hielo Mineral Topical Analgesic Spray